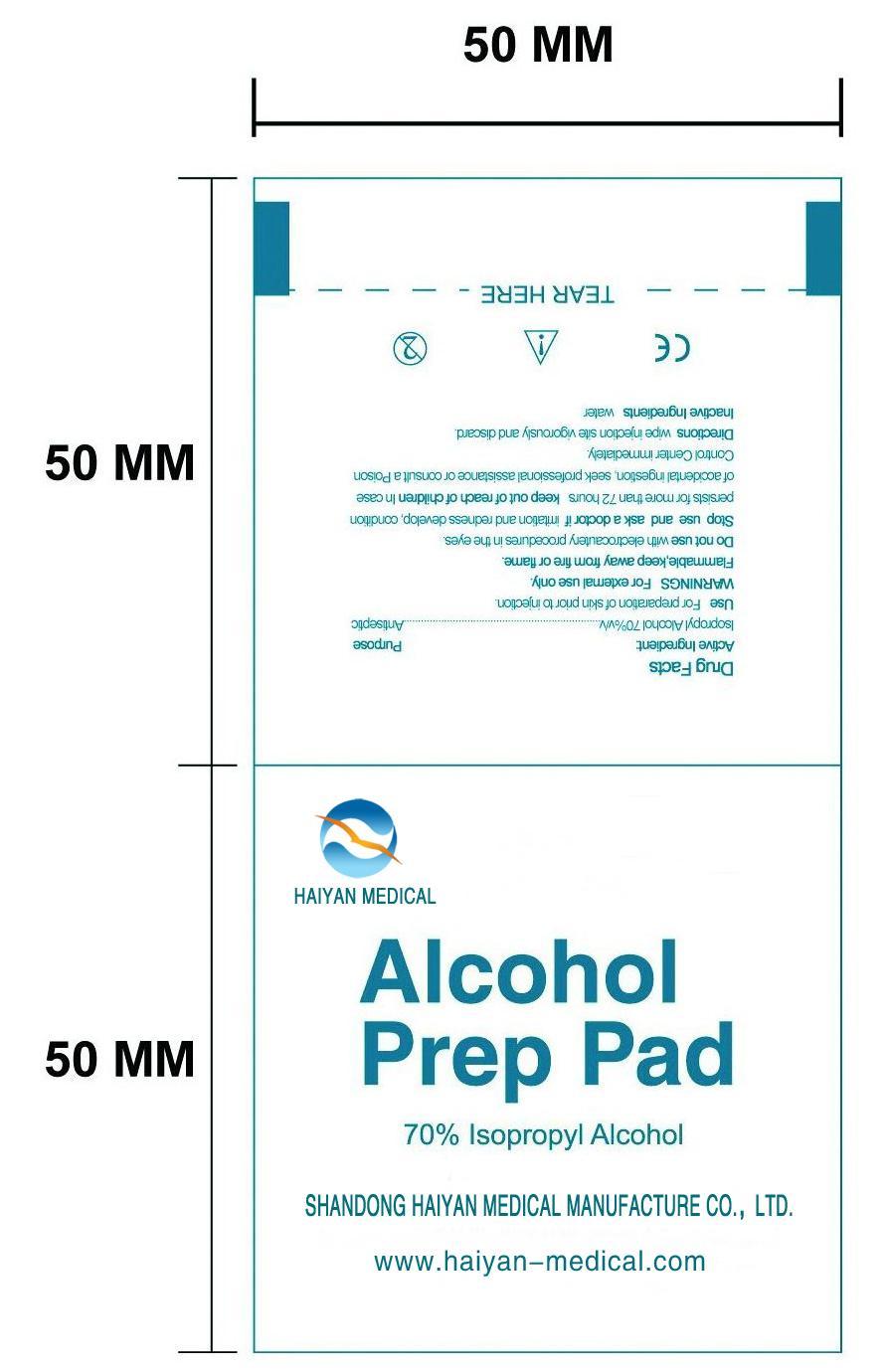 DRUG LABEL: Alcohol Prep Pad
NDC: 42339-001 | Form: SWAB
Manufacturer: Shandong Haiyan Medical Manufacture Co., Ltd.
Category: otc | Type: HUMAN OTC DRUG LABEL
Date: 20220319

ACTIVE INGREDIENTS: ISOPROPYL ALCOHOL 0.7 mL/1 1
INACTIVE INGREDIENTS: WATER

42339-001 Alcohol Prep Pad 70% Isopropyl Alcohol SHANDONG HAIYAN MEDICAL MANUFACTURE CO., LTD. Drug Facts www. haiyan-medical.com

Active Ingredient

Isopropyl Alcohol 70%v/v

Purpose

Antiseptic

Use

For preparation of skin prior to injection.

WARNINGS

For External use only.

Flammable,keep away from fire or flame.

Do not use with electrocautery procedures in eyes.

Stop use and ask a doctor if irritation and redness develop,condition persists for more than 72 hours .

keep out of reach of children

In case of accidental ingestion, seek professional assistance or consult a PoisonControl Center immediately.

Directions

Wipe injection site vigorously and discard.

Inactive ingredients

purified water

PACKAGE LABEL

section text here